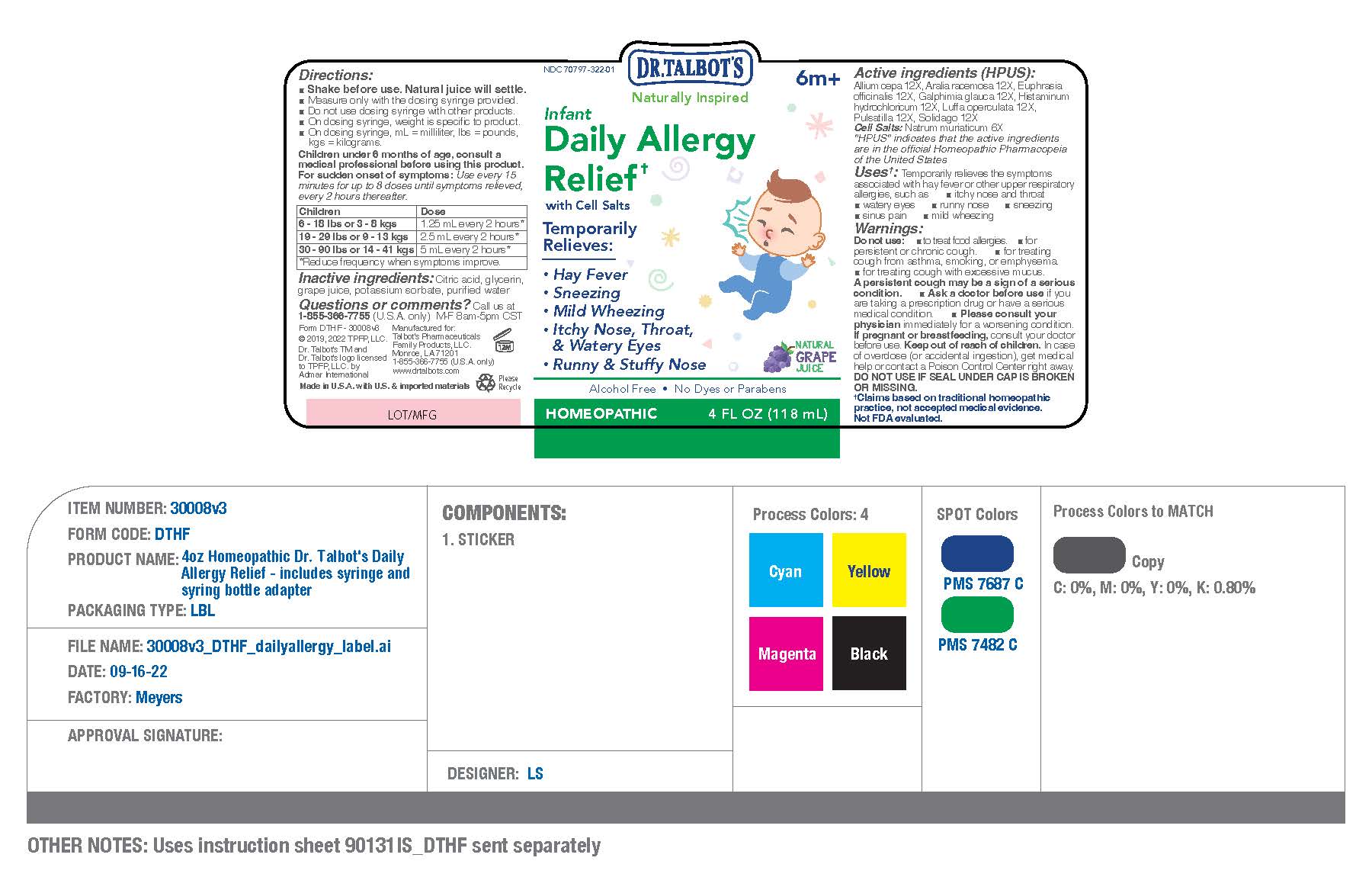 DRUG LABEL: Dr Talbots Infant Daily Allergy Relief
NDC: 70797-322 | Form: LIQUID
Manufacturer: Talbot's Pharmaceuticals Family Products,LLC.
Category: homeopathic | Type: HUMAN OTC DRUG LABEL
Date: 20220912

ACTIVE INGREDIENTS: ARALIA RACEMOSA ROOT 12 [hp_X]/118 mL; EUPHRASIA STRICTA 12 [hp_X]/118 mL; LUFFA OPERCULATA FRUIT 12 [hp_X]/118 mL; ONION 12 [hp_X]/118 mL; ANEMONE PULSATILLA 12 [hp_X]/118 mL; HISTAMINE DIHYDROCHLORIDE 12 [hp_X]/118 mL; SOLIDAGO VIRGAUREA FLOWERING TOP 12 [hp_X]/118 mL; GALPHIMIA GLAUCA FLOWERING TOP 12 [hp_X]/118 mL; SODIUM CHLORIDE 6 [hp_X]/118 mL
INACTIVE INGREDIENTS: GLYCERIN; POTASSIUM SORBATE; CITRIC ACID MONOHYDRATE; WATER; CONCORD GRAPE JUICE

ACTIVE INGREDIENTS

Active ingredients (HPUS)

Allium cepa 12X
Aralia racemosa 12X
Euphrasia officinalis 12X.
Galphimia glauca 12X
Histaminum hydrochloricum 12X
Luffa operculata 12X
Pulsatilla 12X
Solidago 12X

CELL SALTS

Natrum muriaticum 6X

INACTIVE INGREDIENTS

Citric acid, glycerin, grape juice, potassium
sorbate, purified water

PURPOSE

Temporarily Relieves:

- Hay Fever
- Sneezing
- Mild wheezing
- Itchy Nose, Thorat, & Watery Eyes
- Runny & Stuffy Nose

PREGNANCY

If pregnant or breastfeeding, consult your doctor before use.
Keep out of reach of children.

DIRECTIONS

For sudden onset of symptoms:
Use every 15 minutes for up to
8 doses until symptoms relieved,
then every 2 hours thereafter.

Children
6 - 18 lbs
or 3 - 8 kgs
1.25 mL every 2 hours,
reduce frequency when
symptoms improve

Children

19 - 29 lbs
or 9 - 13 kg

2.5 mL every 2 hours,
reduce frequency when
symptoms improve
Children
30 - 90 lbs
or 14 - 41 kgs

5 mL every 2 hours,
reduce frequency when
symptoms improve

QUESTIONS

Questions or comments?
Call us at 1-855-366-7755 (U.S.A. only)
M-F 8am-5pm CST

Ask a doctor before use if you are taking a prescription drug or have a serious medical condition.

Please consult your physician immidiately for a worsening condition.

Warnings

Do not use:

- to treat food allergies
- for persistent or chronic cough
- for treating cough from asthma, smoking, or emphysema
- for treating cough with excessive mucus

A persistent cough may be a sign of a serious condition.

Uses

Temporrarily relieves the symptoms asscociated with hay fever or other upper respiratory allergies, such as

- itchy nose and throat
- watery eyes
- runny nose
- sneezing
- sinus pain
- mild wheezing

Keep Out of Reach of Children

In case of overdose (or accidental ingestion), get medical help or contact a Poison Control center right away.

DO NOT USE IF SEAL UNDER CAP IS BROKEN OR MISSING.

PRINCIPAL DISPLAY